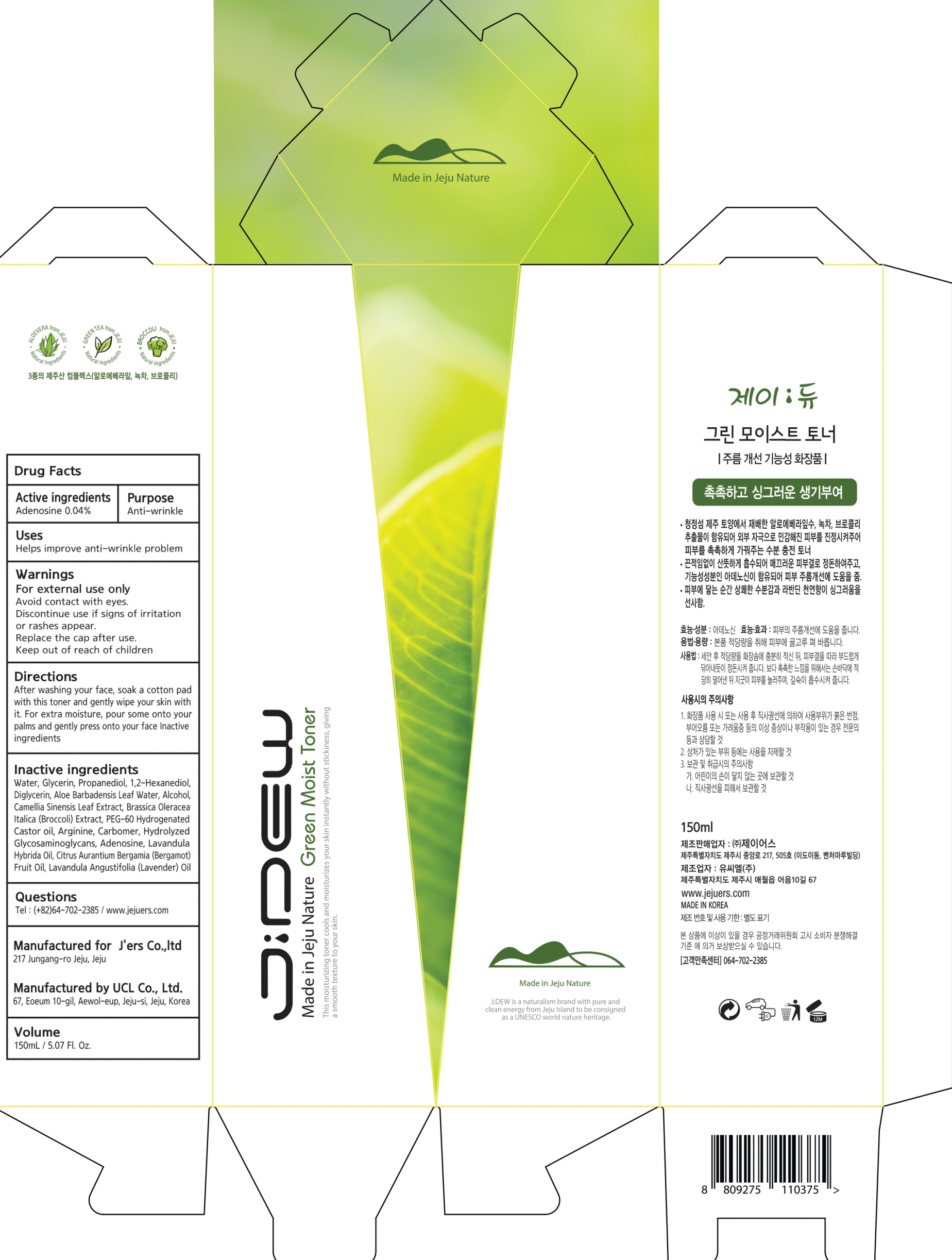 DRUG LABEL: JDEW GREEN MOIST TONER
NDC: 72543-020 | Form: LIQUID
Manufacturer: J'ers Co.,ltd
Category: otc | Type: HUMAN OTC DRUG LABEL
Date: 20180918

ACTIVE INGREDIENTS: Adenosine 0.06 g/150 mL
INACTIVE INGREDIENTS: WATER; GLYCERIN

ACTIVE INGREDIENT

Active ingredients: Adenosine 0.04%

INACTIVE INGREDIENT

Inactive ingredients:

Water, Glycerin, Propanediol, 1,2-Hexanediol, Diglycerin, Aloe Barbadensis Leaf Water, Alcohol, Camellia Sinensis Leaf Extract, Brassica Oleracea Italica (Broccoli) Extract, PEG-60 Hydrogenated Castor oil, Arginine, Carbomer, Hydrolyzed Glycosaminoglycans, Adenosine, Lavandula Hybrida Oil, Citrus Aurantium Bergamia (Bergamot) Fruit Oil, Lavandula Angustifolia (Lavender) Oil

PURPOSE

Purpose: Anti-wrinkle

WARNINGS

- For external use only

- Avoid contact with eyes.

- Discontinue use if signs of irritation or rashes appear.

- Replace the cap after use.

- Keep out of reach of children

KEEP OUT OF REACH OF CHILDREN

Uses

Helps improve anti-wrinkle problem

Directions

After washing your face, soak a cotton pad with this toner and gently wipe your skin with it.

For extra moisture, pour some onto your palms and gently press onto your face.